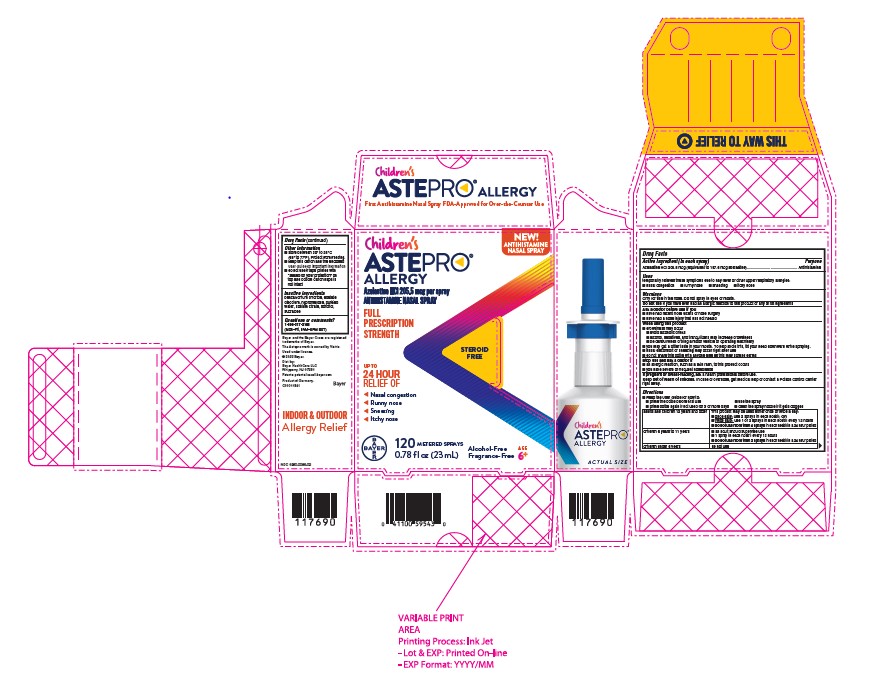 DRUG LABEL: Children Astepro Allergy
NDC: 0280-0066 | Form: SPRAY, METERED
Manufacturer: Bayer HealthCare LLC.
Category: otc | Type: HUMAN OTC DRUG LABEL
Date: 20251204

ACTIVE INGREDIENTS: AZELASTINE HYDROCHLORIDE 205.5 ug/1 1
INACTIVE INGREDIENTS: BENZALKONIUM CHLORIDE; EDETATE DISODIUM; HYPROMELLOSES; SODIUM CITRATE; SORBITOL; SUCRALOSE; WATER

Children's Astepro Allergy

Drug Facts

Active ingredient

Azelastine HCl 205.5 mcg (equivalent to 187.6 mcg azelastine)

Purpose

Antihistamine

Uses

temporarily relieves these symptoms due to hay fever or other upper respiratory allergies:

- nasal congestion
- runny nose
- sneezing
- itchy nose

Warnings

Only for use in the nose. Do not spray in eyes or mouth.

Do not use if you have ever had an allergic reaction to this product or any of its ingredients.

Ask a doctor before use if you

- have had recent nose ulcers or nose surgery
- have had a nose injury that has not healed

When using this product

- drowsiness may occur
- avoid alcoholic drinks
- alcohol, sedatives, and tranquilizers may increase drowsiness
- be careful when driving a motor vehicle or operating machinery
- you may get a bitter taste in your mouth. To help avoid this, tilt your head downward while spraying.
- nasal discomfort or sneezing may occur right after use
- do not share this bottle with anyone else as this may spread germs

Stop use and ask a doctor if

- an allergic reaction, such as a skin rash, to this product occurs
- you have severe or frequent nosebleeds

PREGNANCY OR BREAST FEEDING

If pregnant or breast-feeding, ask a health professional before use.

Keep out of reach of children. In case of overdose, get medical help or contact a Poison Control Center right away.

Directions

Read the User Guide for how to:

- prime the bottle before first use
- prime bottle again if not used for 3 or more days
- use the spray
- clean the spray nozzle if it gets clogged

adults and children 12 years and older | This product may be used either once or twice a day:; - once daily: use 2 sprays in each nostril; OR - twice daily: use 1 or 2 sprays in each nostril every 12 hours - do not use more than 4 sprays in each nostril in a 24 hour period
children 6 years to 11 years | - an adult should supervise use - 1 spray in each nostril every 12 hours - do not use more than 2 sprays in each nostril in a 24 hour period
children under 6 years | do not use

Other information

- store between 20° to 25° C (68° to 77° F). Protect from freezing.
- keep this carton and the enclosed User Guide for important information
- do not use if tape printed with “sealed for your protection” on top and bottom carton flaps is not intact

Inactive ingredients

benzalkonium chloride, edetate disodium, hypromellose, purified water, sodium citrate, sorbitol, sucralose

Questions or comments

1-800-317-2165 (Mon-Fri, 9AM-5PM EST)

PACKAGE LABEL

Azelastine HCl 205.5 mcg per spray

ANTIHISTAMINE NASAL SPRAY

FULL PRESCRIPTION STRENGTH

STEROID FREE

UP TO 24 HOUR RELIEF OF

Nasal congestion
Runny nose
Sneezing
Itchy nose